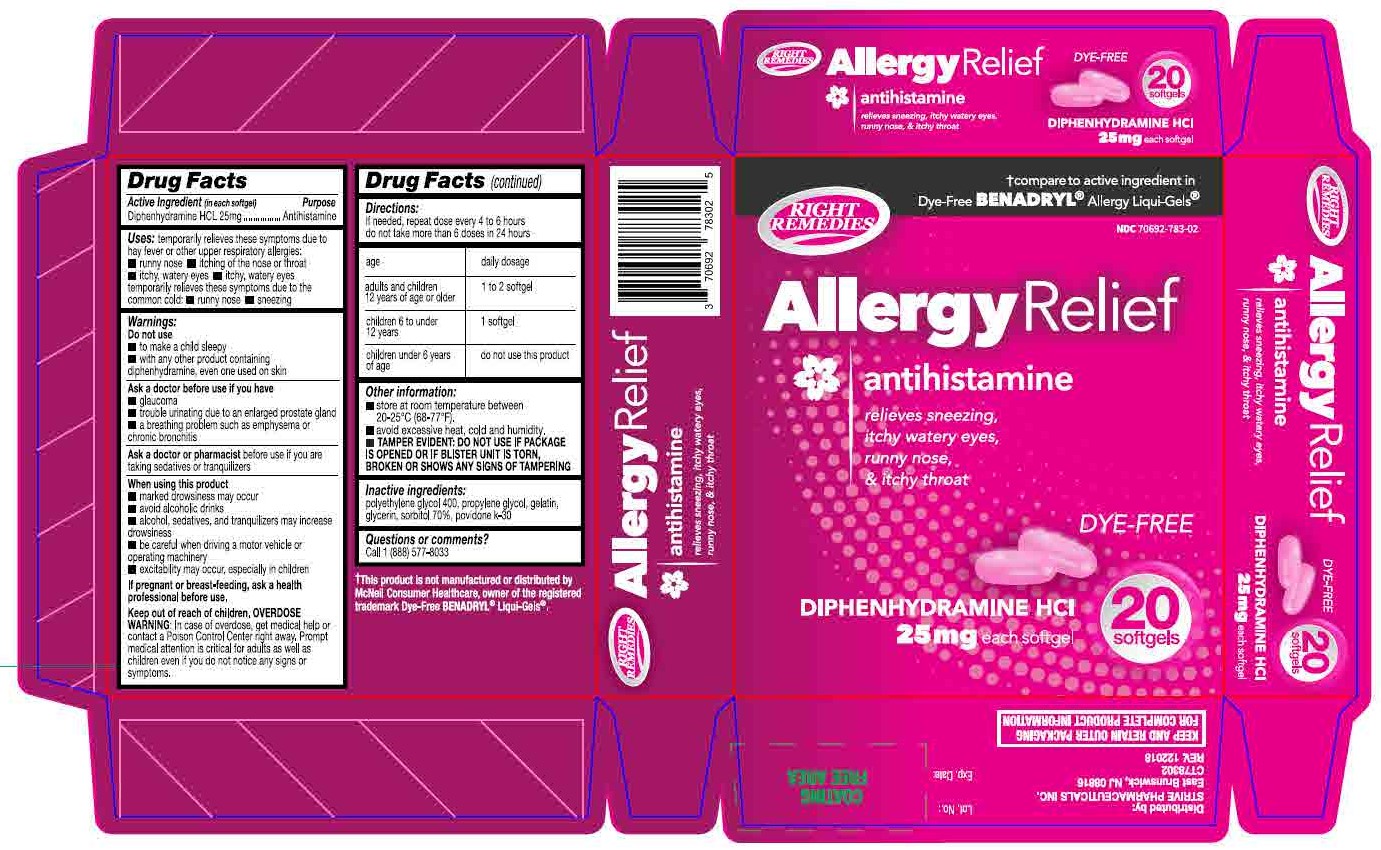 DRUG LABEL: Diphenhydramine Hydrochloride
NDC: 70692-783 | Form: CAPSULE, LIQUID FILLED
Manufacturer: Strive Pharmaceuticals Inc.
Category: otc | Type: HUMAN OTC DRUG LABEL
Date: 20220412

ACTIVE INGREDIENTS: DIPHENHYDRAMINE HYDROCHLORIDE 25 mg/1 1
INACTIVE INGREDIENTS: POLYETHYLENE GLYCOL 400; SORBITOL; PROPYLENE GLYCOL; GLYCERIN; GELATIN; POVIDONE K30

ALLERGY RELIEF
Diphenhydramine HCl 25mg

ACTIVE INGREDIENT

Diphenhydramine HCl 25mg

PURPOSE

Antihistamine

INACTIVE INGREDIENT

polyethylene glycol 400, propylene glycol, gelatin, glycerin, sorbitol 70%, povidone k-30

DOSAGE AND ADMINISTRATION

If needed, repeat dose every 4 to 6 hours donot take more than 6 doses in 24 hours

Age | Daily dosage
Adults and children 12 years of age or older | 1 to 2 softgel
Children 6 to under 12 years | 1 softgel
Children under 6 years of age | do not use this product

INDICATIONS AND USAGE

temporarily relieves these symptoms due to hay fever or other respiratory allergies:

- runny nose
- itching of the nose or throat
- itchy, watery eyes

temporarily relieves these symptoms due to the common cold:

- runny nose
- sneezing

Do not use

- to make a child sleepy
- with any other product containing diphenhydramine, even one used on skin

Ask a doctor before use if you have

- glaucoma
- trouble urinating due to an enlarged prostate gland
- a breathing problem such as emphysema or chronic bronchitis

Ask a doctor or pharmacist before use if you are taking sedatives or tranquilizers

When using this product

- marked drowsiness may occur
- avoid alcoholic drinks
- alcohol, sedatives, and tranquilizers may increase drowsiness
- be careful when driving a motor vehicle or operating machinery
- excitability may occur, expecially in children

If pregnant or breast-feeding, ask a health professional before use.

Keep out of reach of children.

OVERDOSAGE

Overdose Warning: In case of overdose, get medical help or contact a Poison Control Center right away. Prompt medical attention is critical for adults as well as children even if you do not notice any signs or symptoms.

OTHER SAFETY INFORMATION

- store between 20-25°C (68-77ºF), Excursions permitted between 15°C-30°C (59-86ºF).
- TAMPER EVIDENT: DO NOT USE IF PACKAGE IS OPENED OR IF BLISTER UNIT IS TORN, BROKEN OR SHOWS ANY SIGNS OF TAMPERING.